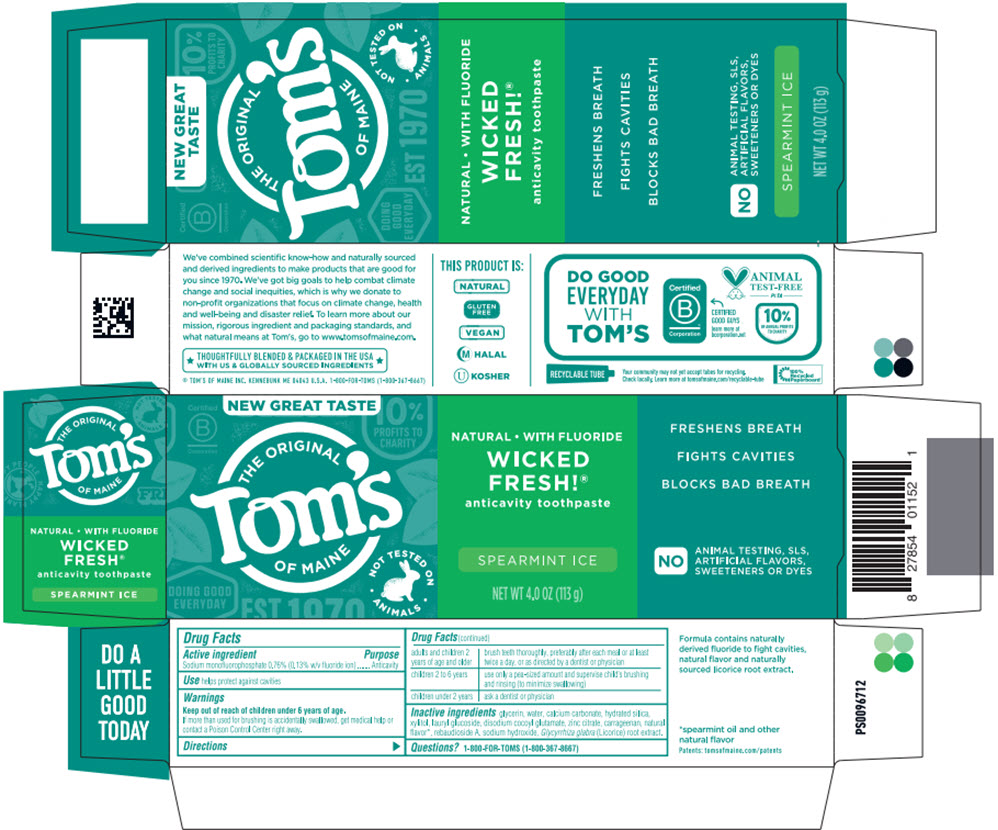 DRUG LABEL: Toms Wicked Fresh SLS-Free Spearmint Ice (SWFT)
NDC: 51009-860 | Form: PASTE, DENTIFRICE
Manufacturer: Tom's of Maine, Inc.
Category: otc | Type: HUMAN OTC DRUG LABEL
Date: 20251224

ACTIVE INGREDIENTS: SODIUM MONOFLUOROPHOSPHATE 1.4 mg/1 g
INACTIVE INGREDIENTS: GLYCERIN; WATER; CALCIUM CARBONATE; HYDRATED SILICA; XYLITOL; LAURYL GLUCOSIDE; DISODIUM COCOYL GLUTAMATE; ZINC CITRATE; .IOTA.-CARRAGEENAN; REBAUDIOSIDE A; SODIUM HYDROXIDE; GLYCYRRHIZA GLABRA

Tom's Wicked Fresh!® SLS-Free Spearmint Ice (SWFT)

Drug Facts

Active ingredient

Sodium monofluorophosphate 0.76% (0.13% w/v fluoride ion)

Purpose

Anticavity

Use

helps protect against cavities

Warnings

Keep out of reach of children under 6 years of age.

If more than used for brushing is accidentally swallowed, get medical help or contact a Poison Control Center right away.

Directions

adults and children 2 years of age and older | brush teeth thoroughly, preferably after each meal or at least twice a day, or as directed by a dentist or physician
children 2 to 6 years | use only a pea-sized amount and supervise child's brushing and rinsing (to minimize swallowing)
children under 2 years | ask a dentist or physician

Inactive ingredients

glycerin, water, calcium carbonate, hydrated silica, xylitol, lauryl glucoside, disodium cocoyl glutamate, zinc citrate, carrageenan, natural flavor [spearmint oil and other natural flavor] , rebaudioside A, sodium hydroxide, Glycyrrhiza glabra (Licorice) root extract.

Questions?

1-800-FOR-TOMS (1-800-367-8667)

PRINCIPAL DISPLAY PANEL - 113 g Tube Carton

NEW GREAT TASTE

THE ORIGINAL
Tom's
OF MAINE

NOT TESTED ON
∙ ANIMALS ∙

NATURAL • WITH FLUORIDE

WICKED
FRESH!®
anticavity toothpaste

SPEARMINT ICE

NET WT 4.0 OZ (113 g)

FRESHENS BREATH

FIGHTS CAVITIES

BLOCKS BAD BREATH

NO
ANIMAL TESTING, SLS
ARTFICIAL FLAVORS,
SWEETENERS OR DYES